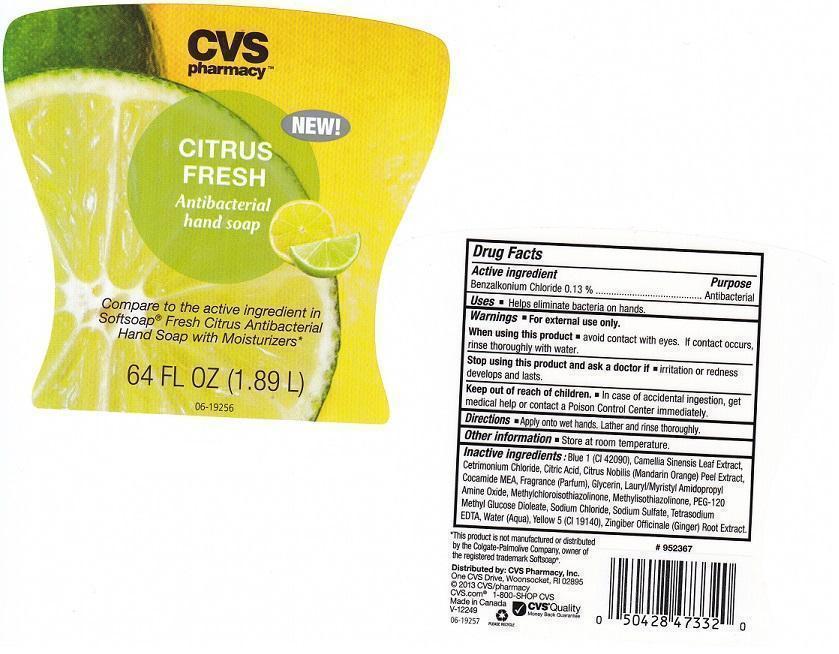 DRUG LABEL: CVS PHARMACY
NDC: 59779-725 | Form: LIQUID
Manufacturer: CVS PHARMACY
Category: otc | Type: HUMAN OTC DRUG LABEL
Date: 20140114

ACTIVE INGREDIENTS: BENZALKONIUM CHLORIDE 1.3 mg/1 mL
INACTIVE INGREDIENTS: FD&C BLUE NO. 1; GREEN TEA LEAF; CETRIMONIUM CHLORIDE; CITRIC ACID MONOHYDRATE; TANGERINE PEEL; COCO MONOETHANOLAMIDE; GLYCERIN; LAURAMIDOPROPYLAMINE OXIDE; METHYLCHLOROISOTHIAZOLINONE; METHYLISOTHIAZOLINONE; PEG-120 METHYL GLUCOSE DIOLEATE; SODIUM CHLORIDE; SODIUM SULFATE; EDETATE SODIUM; WATER; FD&C YELLOW NO. 5; GINGER

DRUG FACTS

ACTIVE INGREDIENT

BENZALKONIUM CHLORIDE 0.13%

PURPOSE

ANTIBACTERIAL

USES

HELPS ELIMINATE BACTERIA ON HANDS

WARNINGS

FOR EXTERNAL USE ONLY

WHEN USING THIS PRODUCT

AVOID CONTACT WITH EYES. IF CONTACT OCCURS, RINSE THOROUGHLY WITH WATER

STOP USING THIS PRODUCT AND ASK A DOCTOR IF

IRRITATION OR REDNESS DEVELOPS AND LASTS

KEEP OUT OF REACH OF CHILDREN

IN CASE OF ACCIDENTAL INGESTION, GET MEDICAL HELP OR CONTACT A POISON CONTROL CENTER IMMEDIATELY

DIRECTIONS

APPLY ONTO WET HANDS. LATHER AND RINSE THOROUGHLY

OTHER INFORMATION

STORE AT ROOM TEMPERATURE

INACTIVE INGREDIENTS

BLUE 1 (CI 42090), CAMELLIA SINENSIS LEAF EXTRACT, CETRIMONIUM CHLORIDE, CITRIC ACID, CITRUS NOBILIS (MANDARIN ORANGE) PEEL EXTRACT, COCAMIDE MEA, FRAGRANCE (PARFUM), GLYCERIN, LAURYL/MYRISTYL AMIDOPROPYL AMINE OXIDE, METHYLCHLOROISOTHIAZOLINONE, METHYLISOTHIAZOLINONE, PEG-120 METHYL GLUCOSE DIOLEATE, SODIUM CHLORIDE, SODIUM SULFATE, TETRASODIUM EDTA, WATER (AQUA), YELLOW 5 (CI 19140), ZINGIBER OFFICINALE (GINGER) ROOT EXTRACT